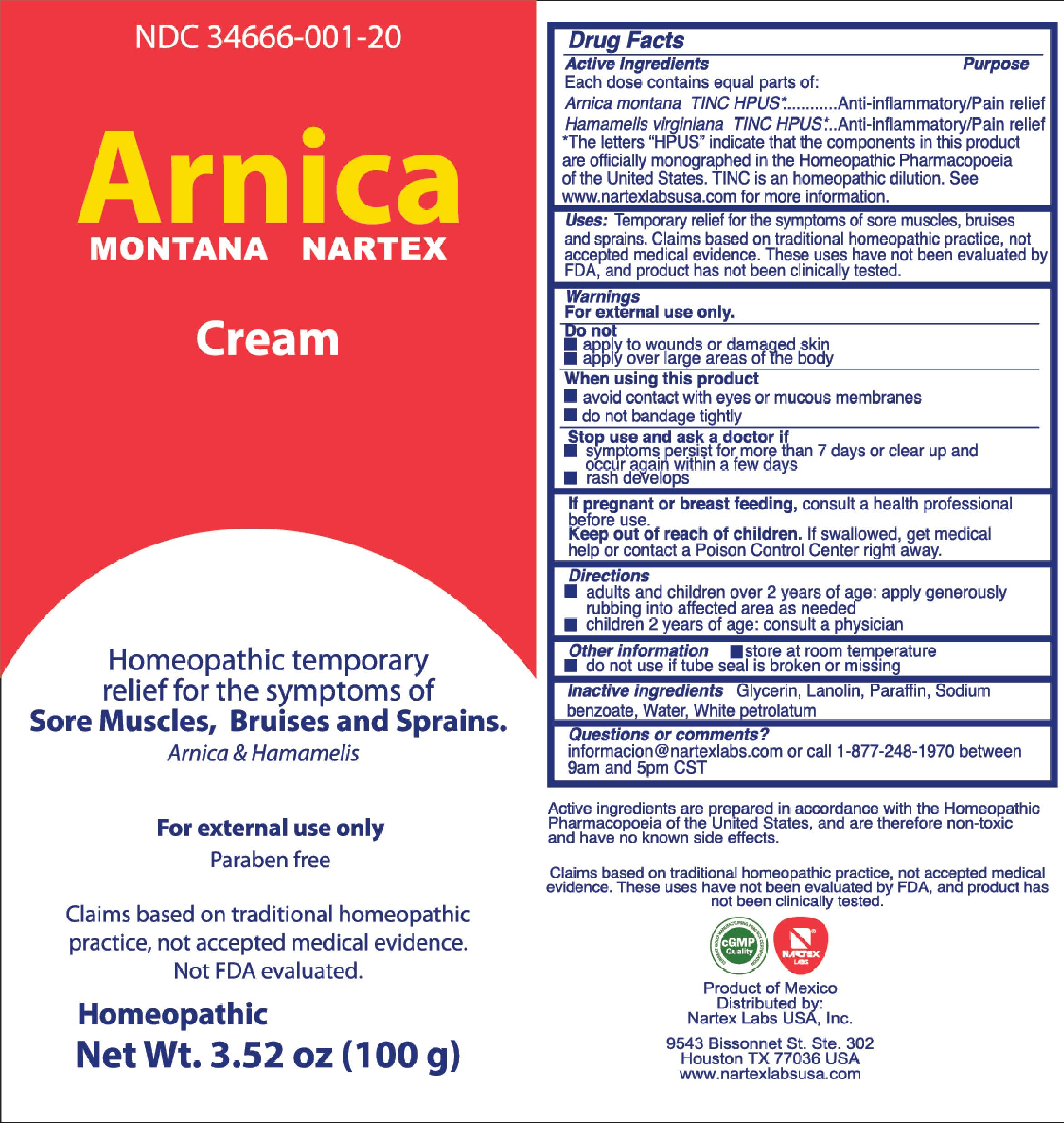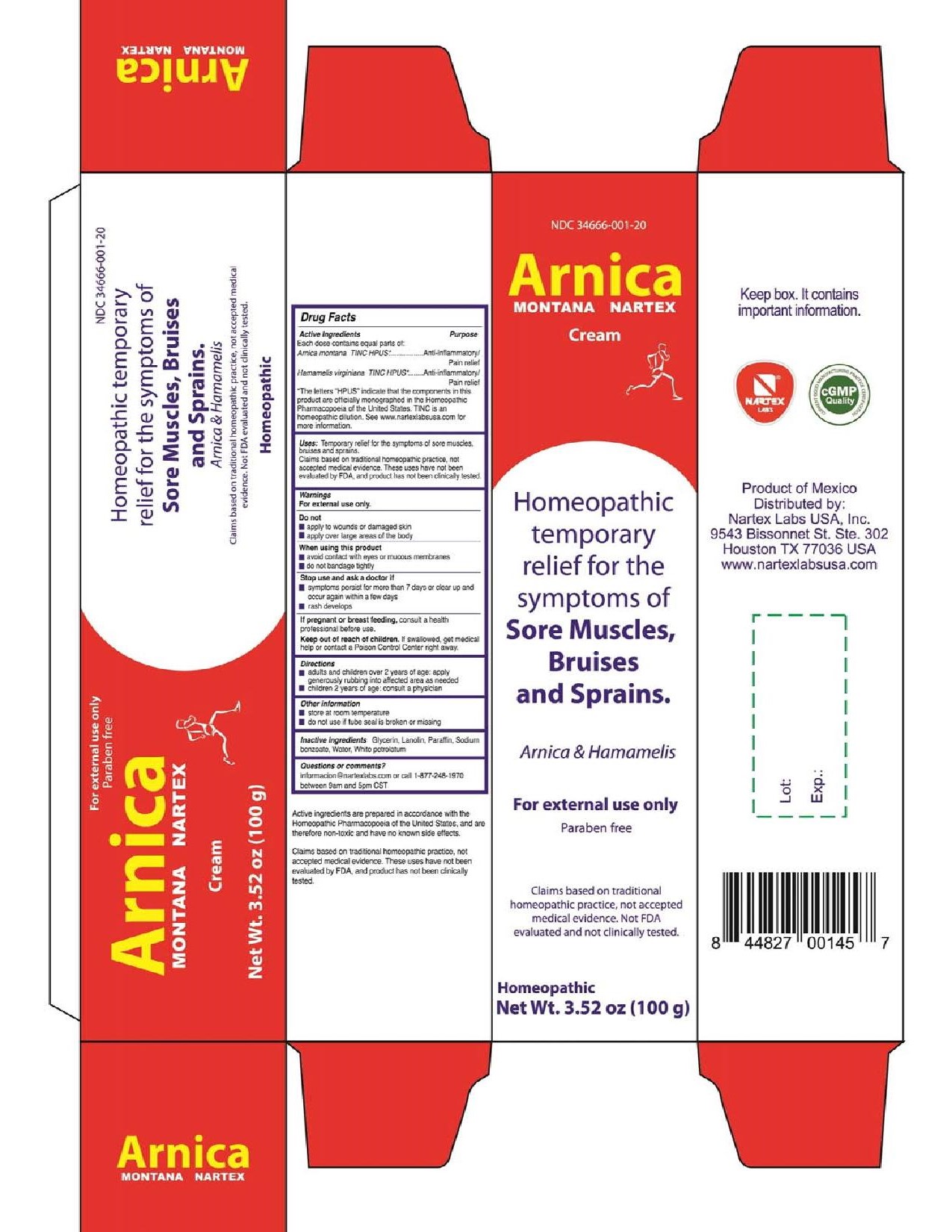 DRUG LABEL: Arnica Montana Nartex
NDC: 34666-001 | Form: CREAM
Manufacturer: NARTEX LABORATORIOS HOMEOPATICOS SA DE CV
Category: homeopathic | Type: HUMAN OTC DRUG LABEL
Date: 20211229

ACTIVE INGREDIENTS: ARNICA MONTANA 1.73 g/29.7 g; HAMAMELIS VIRGINIANA LEAF 0.0178 g/29.7 g
INACTIVE INGREDIENTS: PETROLATUM; LANOLIN; GLYCERIN; PARAFFIN; SODIUM BENZOATE; WATER

Arnica Montana Nartex Cream

Active Ingredients

Each dose contains equal parts of:

Arnica montana TINC HPUS*

Hamamelis virginiana TINC HPUS*

The letters "HPUS" indicate that the components in this product are officially monographed in the Homeopathic Pharmacopoeia of the Untied States. TINC is an homeopathic dilution. See www.nartexlabsusa.com for more information.

Purpose

Arnica montana TINC HPUS*......................Anti-inflammatory/Pain relief
Hamamelis virginiana TINC HPUS*.............Anti-inflammatory/Pain relief

Uses:

Temporary relief for the symptoms of sore muscles, bruises and sprains.
Claims based on traditional homeopathic practice, not accepted medical evidence. These uses have not been evaluated by FDA, and product has not been clinically tested.

Warnings

For external use only.

Do not

- apply to wounds or damaged skin
- apply over large areas of the body

When using this product

- avoid contact with eyes or mucous membranes
- do not bandage tightly

Stop use and ask a doctor if

- symptoms persist for more than 7 days or clear up and occur again within a few days
- rash develops

PREGNANCY OR BREAST FEEDING

If pregnant or breast feeding, consult a health professional before use.

Keep out of reach of children. If swallowed, get medical help or contact a Poison Control Center right away.

OTHER SAFETY INFORMATION

If swallowed, get medical help or contact a Poison Control Center right away.

Directions

- adults and children over 2 years of age: apply generously rubbing into affected area as needed
- children 2 years of age: consult a physician

Other information

- store at room temperature
- do not use if tube seal is broken or missing

Inactive ingredients

Glycerin, Lanolin wax, Paraffin, Sodium benzoate, Water, White petrolatum

Questions or comments?

informacion@nartexlabs.com or call 1-877-248-1970 between 9am and 5pm CST

DESCRIPTION

Active ingredients are prepared in accordance with the Homeopathic Pharmacopoeia of the United States, and are therefore non-toxic and have no known side effects.
Claims based on traditional homeopathic practice, not accepted medical evidence. These uses have not been evaluated by FDA, and product has not been clinically tested.

Principal Display Panel

For external use only

Arnica Montana Nartex Cream

Net Wt. 3.52 oz

Homeopathic temporary relief for the symptoms of Sore Muscles, Bruises and Sprains.

Arnica & Hamamelis

Claims based on traditional homeopathic practice, not accepted medical evidence. Not FDA evaluated.

Homeopathic